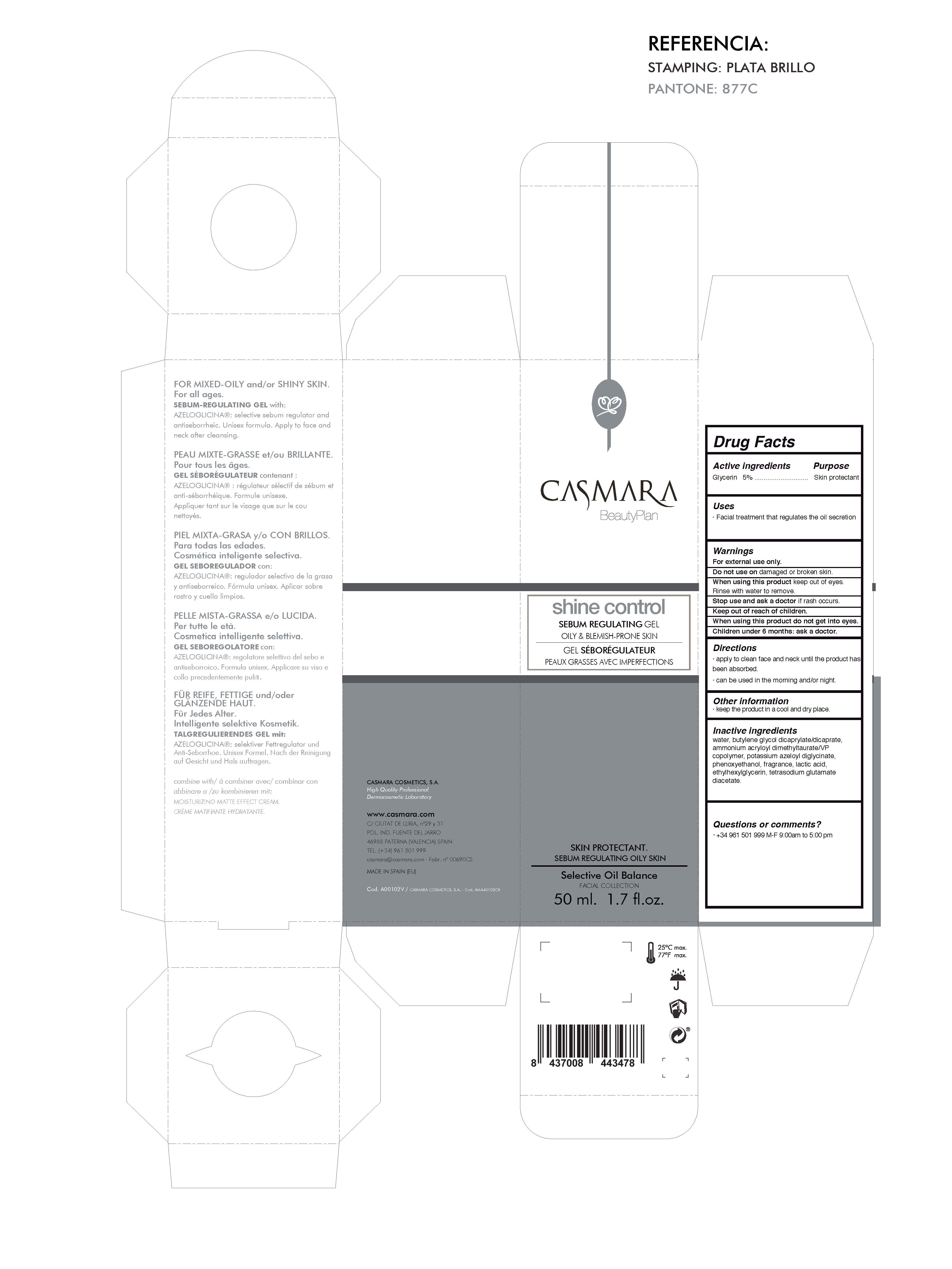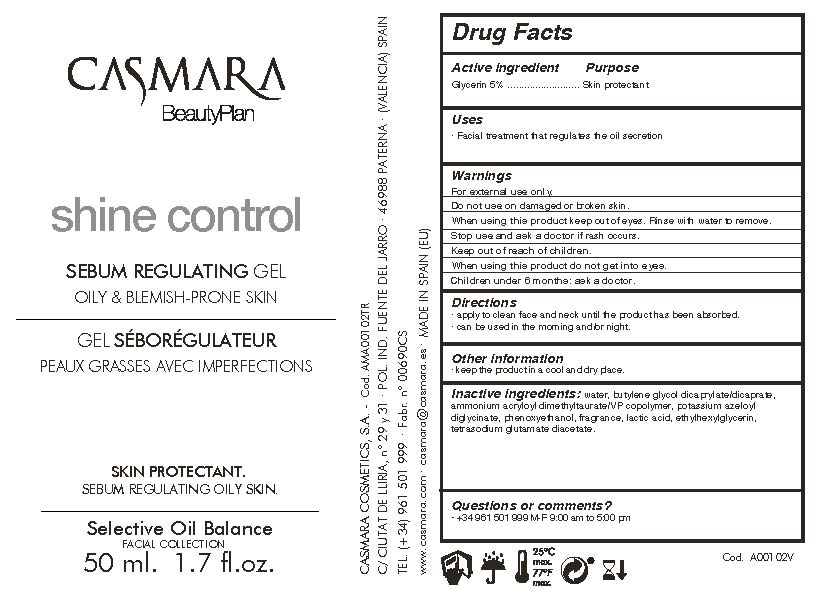 DRUG LABEL: Shine Control Sebum Regulating Gel
NDC: 20151-095 | Form: GEL
Manufacturer: CASMARA COSMETICS, SA
Category: otc | Type: HUMAN OTC DRUG LABEL
Date: 20170226

ACTIVE INGREDIENTS: GLYCERIN 5 mg/1 mL
INACTIVE INGREDIENTS: TETRASODIUM GLUTAMATE DIACETATE 0.094 mg/1 mL; POTASSIUM AZELOYL DIGLYCINATE 1.8 mg/1 mL; WATER 86.81 mg/1 mL; AMMONIUM ACRYLOYLDIMETHYLTAURATE/VP COPOLYMER 2 mg/1 mL; LACTIC ACID 0.14 mg/1 mL; ETHYLHEXYLGLYCERIN 0.1 mg/1 mL; BUTYLENE GLYCOL DICAPRYLATE/DICAPRATE 3 mg/1 mL; PHENOXYETHANOL 0.9 mg/1 mL

Shine Control Sebum Regulating Gel
Oily Blemish Prone Skin

Active Ingredients Purpose

Glycerin 8%.................... Skin Protectant

Uses

. facial treatment that regulates the oil secretion

Uses

. facial treatment that regulates the oil secretion

Warnings

For external use only.

Do not use on damaged or broken skin.

When using this product keep our of the eyes. Rinse with water to remove.

Stop use and ask a doctor if rash occurs.

Keep out of reach of children.

Whhen using this product do not get into eyes.

Children under 6 months: as a doctor.

Keep out of reach of children.

Warnings

Stop use and ask a doctor if rash occurs.

Questions or comments?

(305) 777-0548 M-F 9:00 am to 5:00 pm

Directions

. apply to clean face and neck until the product has been absorbed

. can be used in the morning and/or night

Other information

. keep the product in a cool and dry place.

Inactive ingredients

Water, Butylene glycol dicaprylate/dicaprate, Ammonium acryloyl dimethyltaurate/VP copolymer, Potassium azeloyl diglycinate, Phenoxyethanol, Fragrance, Lactic acid, Ethylhexylglycerin, Tetrasodium glutamate diacetate

Directions

. apply to clean face and neck until the product has been absorbed

. can be used in the morning and/or night

Shine Control

Sebum Regulating Gel

Oily Blemish Prone Skin